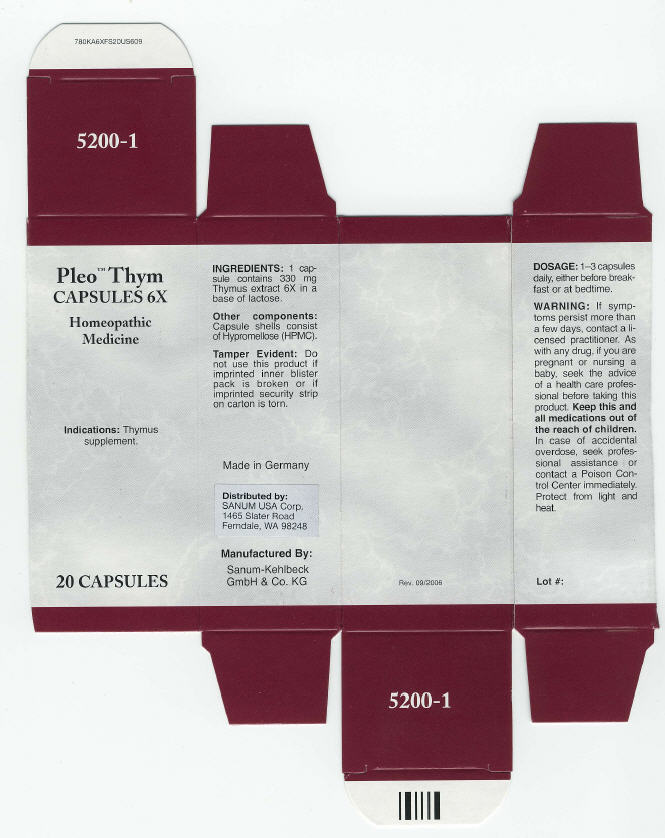 DRUG LABEL: Pleo Thym
NDC: 60681-5200 | Form: CAPSULE
Manufacturer: Sanum Kehlbeck GmbH & Co. KG
Category: homeopathic | Type: HUMAN OTC DRUG LABEL
Date: 20091014

ACTIVE INGREDIENTS: thymus extract 6 [HP_X]/1 1
INACTIVE INGREDIENTS: lactose; hypromellose

Pleo™ Thym
CAPSULES 6X

Homeopathic Medicine

20 CAPSULES

Indications

Thymus supplement.

INGREDIENTS

1 capsule contains 330 mg Thymus extract 6X in a base of lactose.

Other components

Capsule shells consist of Hypromellose (HPMC).

Tamper Evident

Do not use this product if imprinted inner blister pack is broken or if imprinted security strip on carton is torn.

DOSAGE

1–3 capsules daily, either before breakfast or at bedtime.

WARNING

If symptoms persist more than a few days, contact a licensed practitioner. As with any drug, if you are pregnant or nursing a baby, seek the advice of a health care professional before taking this product.

KEEP OUT OF REACH OF CHILDREN

Keep this and all medications out of the reach of children. In case of accidental overdose, seek professional assistance or contact a Poison Control Center immediately.

STORAGE AND HANDLING

Protect from light and heat.

Made in Germany

Distributed by:
SANUM USA Corp.
1465 Slater Road
Ferndale, WA 98248

Manufactured By:
Sanum-Kehlbeck
GmbH & Co. KG

Rev. 09/2006

PRINCIPAL DISPLAY PANEL - 20 Capsule Carton

Pleo™ Thym
CAPSULES 6X

Homeopathic
Medicine

Indications: Thymus
supplement.

20 CAPSULES